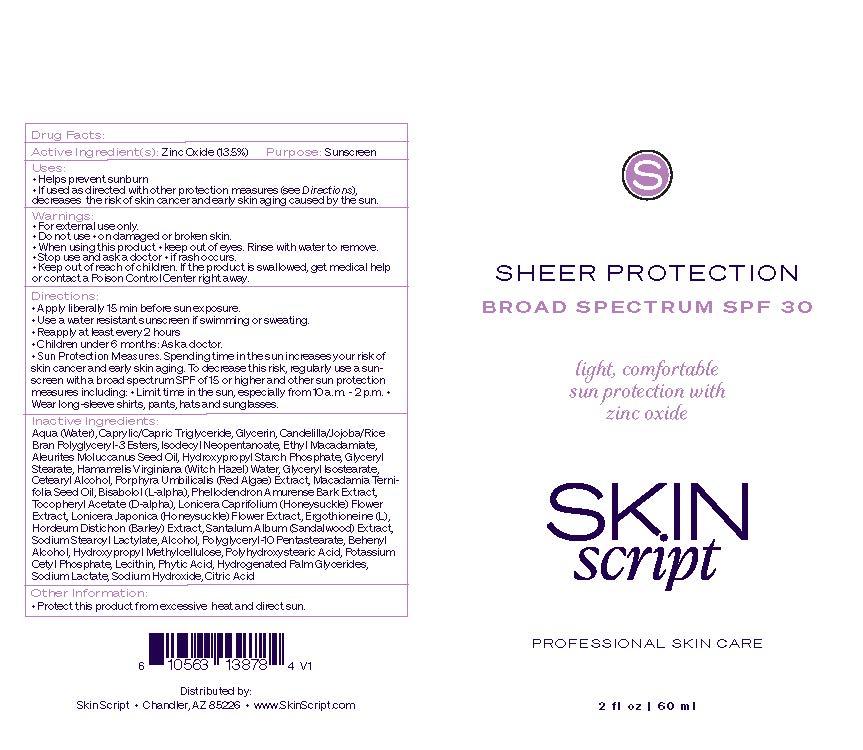 DRUG LABEL: Sheer Protection SPF 30
NDC: 83657-610 | Form: CREAM
Manufacturer: Skin Script, LLC
Category: otc | Type: HUMAN OTC DRUG LABEL
Date: 20251229

ACTIVE INGREDIENTS: ZINC OXIDE 0.0135 g/1 g
INACTIVE INGREDIENTS: SIMMONDSIA CHINENSIS SEED WAX; LONICERA JAPONICA FLOWER; ETHYL MACADAMIATE; PORPHYRA UMBILICALIS; PHELLODENDRON AMURENSE BARK; GLYCERYL ISOSTEARATE; .ALPHA.-TOCOPHEROL ACETATE, D-; LECITHIN, SOYBEAN; SODIUM HYDROXIDE; HYDROGENATED PALM GLYCERIDES; ALCOHOL; DOCOSANOL; HYPROMELLOSES; SODIUM LACTATE; CITRIC ACID MONOHYDRATE; LEVOMENOL; SANDALWOOD; LONICERA CAPRIFOLIUM FLOWER; POTASSIUM CETYL PHOSPHATE; CETOSTEARYL ALCOHOL; WATER; GLYCERIN; SODIUM STEAROYL LACTYLATE; POLYHYDROXYSTEARIC ACID (2300 MW); BARLEY; ISODECYL NEOPENTANOATE; HYDROXYPROPYL CORN STARCH (5% SUBSTITUTION BY WEIGHT); MACADAMIA OIL; FYTIC ACID; ERGOTHIONEINE; GLYCERYL MONOSTEARATE; HAMAMELIS VIRGINIANA TOP WATER; MEDIUM-CHAIN TRIGLYCERIDES; RICE BRAN; CANDELILLA WAX; POLYGLYCERIN-3; POLYGLYCERYL-10 PENTASTEARATE; KUKUI NUT OIL

Active Ingredient(s): Zinc Oxide (13.5%)

Purpose: Sunscreen

- Keep out of reach of children. If the product is swallowed, get medical help or contact a Posion Control center right away.

Uses:

- Helps prevent sunburn
- If used as directed with other protection measures (see Directions), decreases the risk of skin cancer and early skin aging caused by the sun.

Warnings:

- For external use only.
- Do not use on damaged or broken skin.
- When using this product keep out of eyes. Rinse with water to remove.
- Stop use and ask a doctor if rash occurs.
- Keep out of reach of children. If the product is swallowed, get medical help or contact a Posion Control Center right away.

Directions:

- Apply liberally 15 min before sun exposure.
- Use a water resistant sunscreen if swimming or sweating.
- Reapply at least every 2 hours
- Children under 6 months: Ask a doctor.
- Sun Protection Measures. Spending time in the sun increases your risk of skin cancer and early skin aging. To decrease this risk, regularly use a sunscreen with a broad spectrum SPF of 15 or higher and other sun protection measures including: Limit time in the sun, especially from 10am - 2pm. Wear long sleeve shirts, pants, hats, and sunglasses.

INACTIVE INGREDIENT

Inactive Ingredients: Aqua (Water), Caprylic/Capric Triglyceride, Glycerin, Candelilla/Jojoba/Rice Bran Polyglyceryl-3 Esters, Isodecyl Neopentanoate, Ethyl Macadamiate, Aleurites Moluccanus Seed Oil, Hydroxypropyl Starch Phosphate, Glyceryl Stearate, Hamamelis Virginiana (Witch Hazel) Water, Glyceryl Isostearate, Cetearyl Alcohol, Porphyra Umbilicalis (Red Algae) Extract, Macadamia Ternifolia Seed Oil, Bisabolol (L-alpha), Phellodendron Amurense Bark Extract, Tocopheryl Acetate (D-alpha), Lonicera Caprifolium (Honeysuckle) Flower Extract, Lonicera Japonica (Honeysuckle) Flower Extract, Ergothioneine (L), Hordeum Distichon (Barley) Extract, Santalum Album (Sandalwood) Extract, Sodium Stearoyl Lactylate, Alcohol, Polyglyceryl-10 Pentastearate, Behenyl Alcohol, Hydroxypropyl Methylcellulose, Polyhydroxystearic Acid, Potassium Cetyl Phosphate, Lecithin, Phytic Acid, Hydrogenated Palm Glycerides, Sodium Lactate, Sodium Hydroxide, Citric Acid

Other Information:

- Protect the product from excessive heat and direct sun.